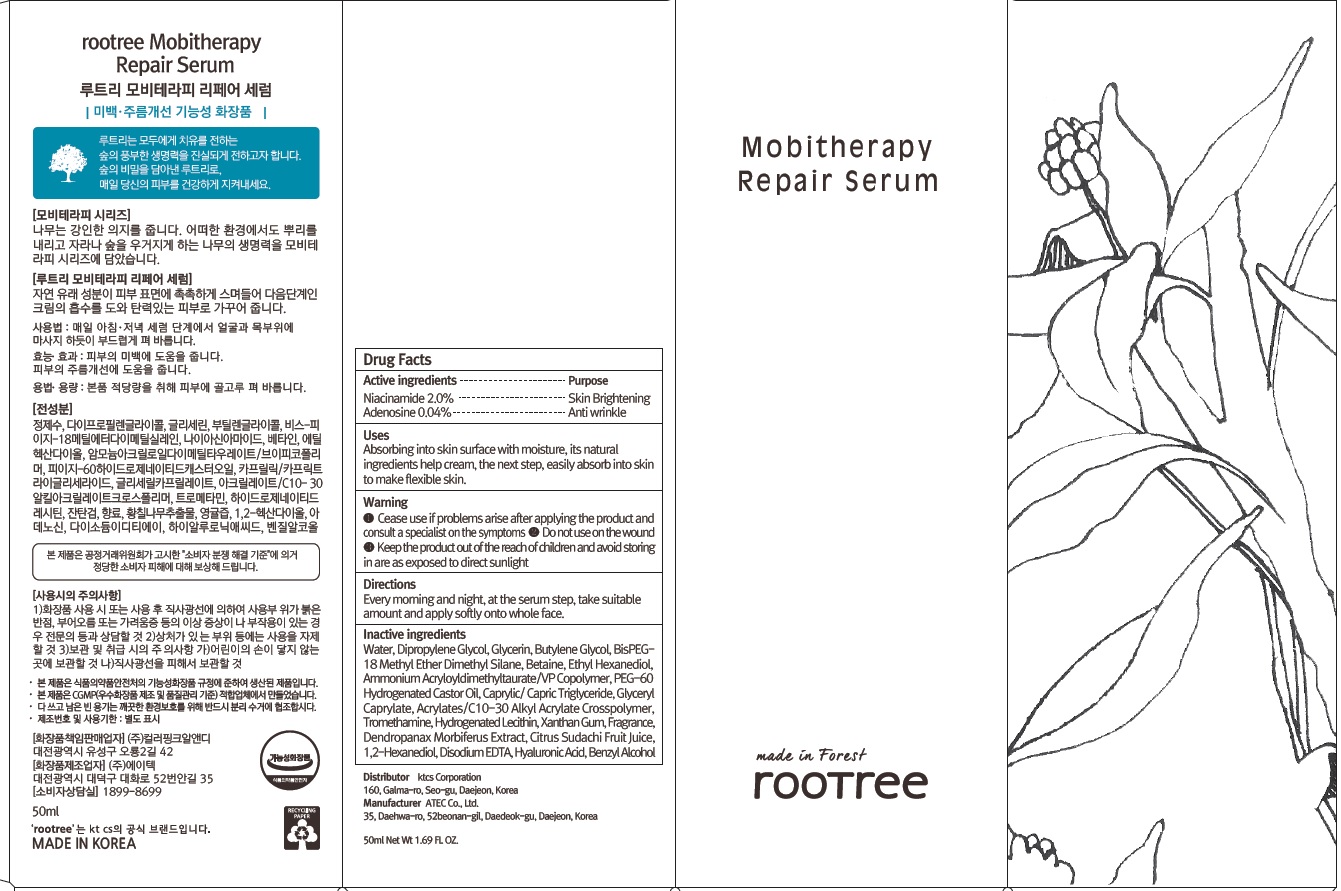 DRUG LABEL: rootree Mobitherapy Repair Serum
NDC: 72441-040 | Form: CREAM
Manufacturer: KTCS Corporation
Category: otc | Type: HUMAN OTC DRUG LABEL
Date: 20201229

ACTIVE INGREDIENTS: Niacinamide 1.0 g/50 mL; Adenosine 0.02 g/50 mL
INACTIVE INGREDIENTS: Water; Dipropylene Glycol

ACTIVE INGREDIENTS

Niacinamide 2.0%, Adenosine 0.04%

INACTIVE INGREDIENTS

Water, Dipropylene Glycol, Glycerin, Butylene Glycol, BisPEG-18 Methyl Ether Dimethyl Silane, Betaine, Ethyl Hexanediol, Ammonium Acryloyldimethyltaurate/VP Copolymer, PEG-60 Hydrogenated Castor Oil, Caprylic/ Capric Triglyceride, Glyceryl Caprylate, Acrylates/C10-30 Alkyl Acrylate Crosspolymer, Tromethamine, Hydrogenated Lecithin, Xanthan Gum, Fragrance, Dendropanax Morbiferus Extract, Citrus Sudachi Fruit Juice, 1,2-Hexanediol, Disodium EDTA, Hyaluronic Acid, Benzyl Alcohol

PURPOSE

Skin Brightening, Anti-wrinkle

WARNINGS

- Cease use if problems arise after applying the product and consult a specialist on the symptoms.

- Do not use on the wound.
- Keep the product out of the reach of children and avoid storing in are as exposed to direct sunlight.

KEEP OUT OF REACH OF CHILDREN

Keep the product out of the reach of children

Uses

Absorbing into skin surface with moisture, its natural ingredients help cream, the next step, easily absorb into skin to make flexible skin.

Directions

Every morning and night, at the serum step, take suitable amount and apply softly onto whole face.